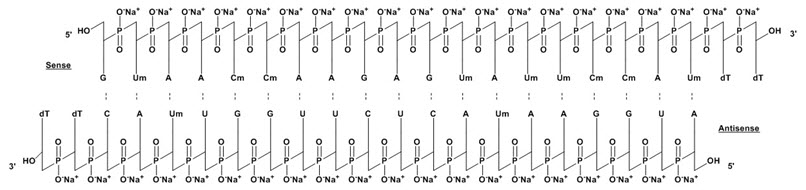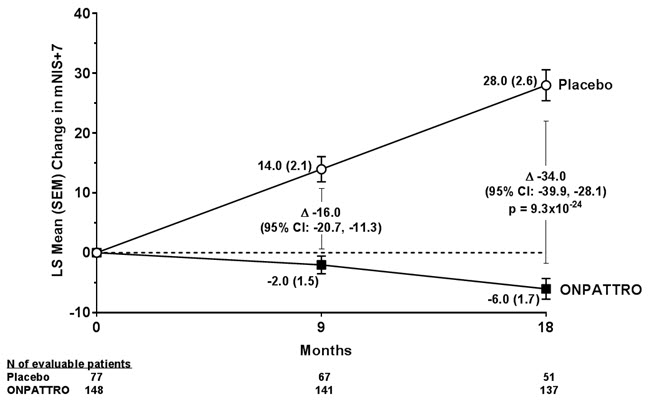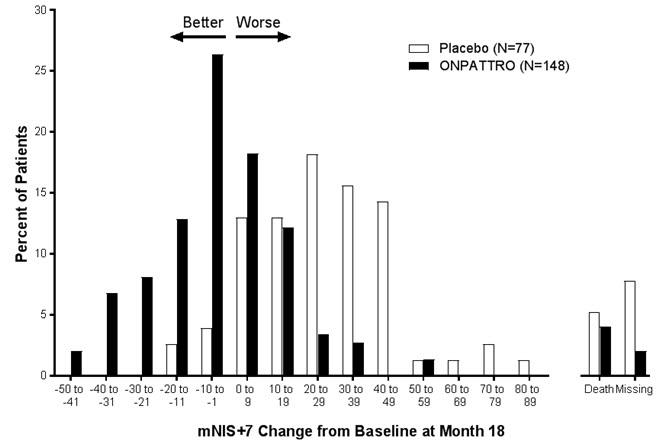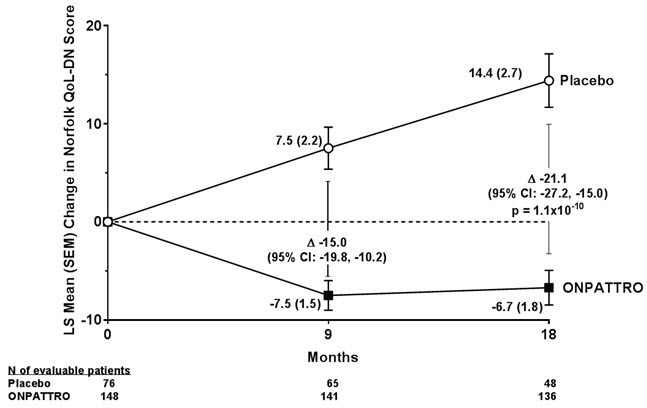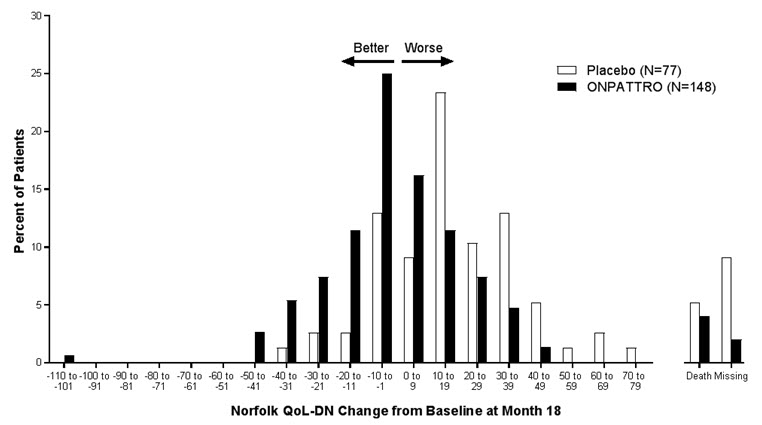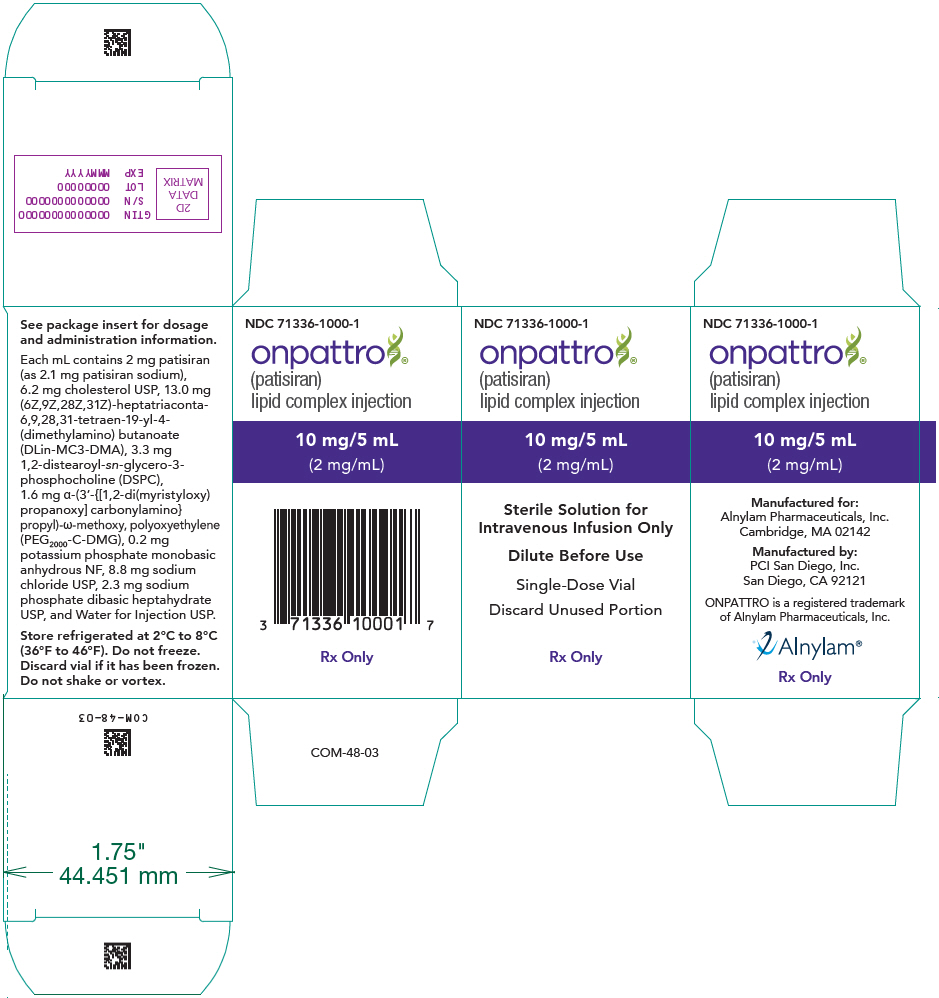 DRUG LABEL: Onpattro
NDC: 71336-1000 | Form: INJECTION, LIPID COMPLEX
Manufacturer: Alnylam Pharmaceuticals, Inc.
Category: prescription | Type: HUMAN PRESCRIPTION DRUG LABEL
Date: 20250908

ACTIVE INGREDIENTS: patisiran sodium 2 mg/1 mL
INACTIVE INGREDIENTS: MC-3 13 mg/1 mL; 1,2-DIMYRISTOYL-SN-GLYCERO-3-CARBOXAMINOPROPYLPOLYETHYLENE GLYCOL 2000 METHYL ETHER 1.6 mg/1 mL; 1,2-Distearoyl-sn-glycero-3-phosphocholine 3.3 mg/1 mL; Cholesterol 6.2 mg/1 mL; Sodium phosphate, dibasic, heptahydrate 2.3 mg/1 mL; MONOBASIC POTASSIUM PHOSPHATE 0.2 mg/1 mL; Sodium Chloride 8.8 mg/1 mL; Water

HIGHLIGHTS OF PRESCRIBING INFORMATION

These highlights do not include all the information needed to use ONPATTRO® safely and effectively. See full prescribing information for ONPATTRO.
ONPATTRO (patisiran) lipid complex injection, for intravenous use
Initial U.S. Approval: 2018

1 INDICATIONS AND USAGE

ONPATTRO contains a transthyretin-directed small interfering RNA and is indicated for the treatment of the polyneuropathy of hereditary transthyretin-mediated amyloidosis in adults.

2 DOSAGE AND ADMINISTRATION

- For patients weighing less than 100 kg, the recommended dosage is 0.3 mg/kg every 3 weeks by intravenous infusion. For patients weighing 100 kg or more, the recommended dosage is 30 mg (2.1)
- Premedicate with a corticosteroid, acetaminophen, and antihistamines (2.2)
- Filter and dilute prior to administration (2.3)
- Infuse over approximately 80 minutes (2.4)

3 DOSAGE FORMS AND STRENGTHS

Lipid Complex Injection: 10 mg/5 mL (2 mg/mL) in a single-dose vial

4 CONTRAINDICATIONS

None

5 WARNINGS AND PRECAUTIONS

- Infusion-related reactions: Monitor for signs and symptoms during infusion. Slow or interrupt the infusion if clinically indicated. Discontinue the infusion if a serious or life-threatening infusion-related reaction occurs (5.1)
- Reduced serum vitamin A levels and recommended supplementation: Supplement with the recommended daily allowance of vitamin A. Refer to an ophthalmologist if ocular symptoms suggestive of vitamin A deficiency occur (5.2)

6 ADVERSE REACTIONS

The most frequently reported adverse reactions (that occurred in at least 10% of ONPATTRO-treated patients and at least 3% more frequently than on placebo) were upper respiratory tract infections and infusion-related reactions (6.1)

To report SUSPECTED ADVERSE REACTIONS, contact Alnylam Pharmaceuticals at 1-877-256-9526 or FDA at 1-800-FDA-1088 or www.fda.gov/medwatch.

FULL PRESCRIBING INFORMATION

1 INDICATIONS AND USAGE

ONPATTRO is indicated for the treatment of the polyneuropathy of hereditary transthyretin-mediated amyloidosis in adults.

2 DOSAGE AND ADMINISTRATION

2.1 Dosing Information

ONPATTRO should be administered by a healthcare professional.

ONPATTRO is administered via intravenous (IV) infusion. Dosing is based on actual body weight.

For patients weighing less than 100 kg, the recommended dosage is 0.3 mg/kg once every 3 weeks.

For patients weighing 100 kg or more, the recommended dosage is 30 mg once every 3 weeks.

Missed Dose

If a dose is missed, administer ONPATTRO as soon as possible.

- If ONPATTRO is administered within 3 days of the missed dose, continue dosing according to the patient's original schedule.
- If ONPATTRO is administered more than 3 days after the missed dose, continue dosing every 3 weeks thereafter.

2.2 Required Premedication

All patients should receive premedication prior to ONPATTRO administration to reduce the risk of infusion-related reactions (IRRs) [see Warnings and Precautions (5.1)]. Each of the following premedications should be given on the day of ONPATTRO infusion at least 60 minutes prior to the start of infusion:

- Intravenous corticosteroid (e.g., dexamethasone 10 mg, or equivalent)
- Oral acetaminophen (500 mg)
- Intravenous H1 blocker (e.g., diphenhydramine 50 mg, or equivalent)
- Intravenous H2 blocker (e.g., famotidine 20 mg, or equivalent)

For premedications not available or not tolerated intravenously, equivalents may be administered orally.

For patients who are tolerating their ONPATTRO infusions but experiencing adverse reactions related to the corticosteroid premedication, the corticosteroid may be reduced by 2.5 mg increments to a minimum dose of 5 mg of dexamethasone (intravenous), or equivalent.

Some patients may require additional or higher doses of one or more of the premedications to reduce the risk of IRRs [see Warnings and Precautions (5.1)].

2.3 Preparation Instructions

ONPATTRO must be filtered and diluted prior to intravenous infusion. The diluted solution for infusion should be prepared by a healthcare professional using aseptic technique as follows:

- Remove ONPATTRO from the refrigerator and allow to warm to room temperature. Do not shake or vortex.
- Inspect visually for particulate matter and discoloration. Do not use if discoloration or foreign particles are present. ONPATTRO is a white to off-white, opalescent, homogeneous solution. A white to off-white coating may be observed on the inner surface of the vial, typically at the liquid-headspace interface. Product quality is not impacted by presence of the white to off-white coating.
- Calculate the required dose of ONPATTRO based on the recommended weight-based dosage [see Dosage and Administration (2.1)].
- Withdraw the entire contents of one or more vials into a single sterile syringe.
- Filter ONPATTRO through a sterile 0.45 micron polyethersulfone (PES) syringe filter into a sterile container.
- Withdraw the required volume of filtered ONPATTRO from the sterile container using a sterile syringe.
- Dilute the required volume of filtered ONPATTRO into an infusion bag containing 0.9% Sodium Chloride Injection, USP for a total volume of 200 mL. Use infusion bags that are di(2-ethylhexyl)phthalate-free (DEHP-free).
- Gently invert the bag to mix the solution. Do not shake. Do not mix or dilute with other drugs.
- Discard any unused portion of ONPATTRO.
- ONPATTRO does not contain preservatives. The diluted solution should be administered immediately after preparation. If not used immediately, store in the infusion bag at room temperature (up to 30°C [86°F]) for up to 16 hours (including infusion time). Do not freeze.

2.4 Infusion Instructions

- Use a dedicated line with an infusion set containing a 1.2 micron polyethersulfone (PES) in-line infusion filter. Use infusion sets and lines that are DEHP-free.
- Infuse the diluted solution of ONPATTRO intravenously, via an ambulatory infusion pump, over approximately 80 minutes, at an initial infusion rate of approximately 1 mL/min for the first 15 minutes, then increase to approximately 3 mL/min for the remainder of the infusion. The duration of infusion may be extended in the event of an IRR [see Warnings and Precautions (5.1)].
- Administer only through a free-flowing venous access line. Monitor the infusion site for possible infiltration during drug administration. Suspected extravasation should be managed according to local standard practice for non-vesicants.
- Observe the patient during the infusion and, if clinically indicated, following the infusion [see Warnings and Precautions (5.1)].
- After completion of the infusion, flush the intravenous administration set with 0.9% Sodium Chloride Injection, USP to ensure that all ONPATTRO has been administered.

3 DOSAGE FORMS AND STRENGTHS

Lipid Complex Injection: 10 mg/5 mL (2 mg/mL) white to off-white, opalescent, homogeneous solution in a single-dose vial.

4 CONTRAINDICATIONS

None.

5 WARNINGS AND PRECAUTIONS

5.1 Infusion-Related Reactions

Infusion-related reactions (IRRs) have been observed in patients treated with ONPATTRO. In clinical studies, all patients received premedication with a corticosteroid, acetaminophen, and antihistamines (H1 and H2 blockers) to reduce the risk of IRRs. In a controlled clinical study, 19% of ONPATTRO-treated patients experienced IRRs, compared to 9% of placebo-treated patients. Among ONPATTRO-treated patients who experienced an IRR, 79% experienced the first IRR within the first 2 infusions. The frequency of IRRs decreased over time. IRRs led to infusion interruption in 5% of patients. IRRs resulted in permanent discontinuation of ONPATTRO in less than 1% of patients in clinical studies. Across clinical studies, the most common symptoms (reported in greater than 2% of patients) of IRRs with ONPATTRO were flushing, back pain, nausea, abdominal pain, dyspnea, and headache [see Adverse Reactions (6.1)]. Severe hypotension and syncope have been reported as symptoms of IRRs in the expanded access program and postmarketing setting.

Patients should receive premedications on the day of ONPATTRO infusion, at least 60 minutes prior to the start of infusion [see Dosage and Administration (2.2)]. Monitor patients during the infusion for signs and symptoms of IRRs. If an IRR occurs, consider slowing or interrupting the ONPATTRO infusion and instituting medical management (e.g., corticosteroids or other symptomatic treatment), as clinically indicated. If the infusion is interrupted, consider resuming at a slower infusion rate only if symptoms have resolved. In the case of a serious or life-threatening IRR, the infusion should be discontinued and not resumed.

Some patients who experience IRRs may benefit from a slower infusion rate or additional or higher doses of one or more of the premedications with subsequent infusions to reduce the risk of IRRs [see Dosage and Administration (2.2)].

5.2 Reduced Serum Vitamin A Levels and Recommended Supplementation

ONPATTRO treatment leads to a decrease in serum vitamin A levels. Supplementation at the recommended daily allowance of vitamin A is advised for patients taking ONPATTRO. Higher doses than the recommended daily allowance of vitamin A should not be given to try to achieve normal serum vitamin A levels during treatment with ONPATTRO, as serum vitamin A levels do not reflect the total vitamin A in the body.

Patients should be referred to an ophthalmologist if they develop ocular symptoms suggestive of vitamin A deficiency (e.g., night blindness).

6 ADVERSE REACTIONS

The following clinically significant adverse reactions are described elsewhere in the labeling:

- Infusion-Related Reactions [see Warnings and Precautions (5.1)]

6.1 Clinical Trials Experience

Because clinical studies are conducted under widely varying conditions, adverse reaction rates observed in the clinical studies of ONPATTRO cannot be directly compared to rates in the clinical studies of another drug and may not reflect the rates observed in practice.

A total of 224 patients with polyneuropathy caused by hereditary transthyretin-mediated amyloidosis (hATTR amyloidosis) received ONPATTRO in the placebo-controlled and open-label clinical studies, including 186 patients exposed for at least 1 year, 137 patients exposed for at least 2 years, and 52 patients exposed for at least 3 years. In the placebo-controlled study, 148 patients received ONPATTRO for up to 18 months (mean exposure 17.7 months). Baseline demographic and disease characteristics were generally similar between treatment groups. The median age of study patients was 62 years and 74% were male. Seventy-two percent of study patients were Caucasian, 23% were Asian, 2% were Black, and 2% were reported as other. At baseline, 46% of patients were in Stage 1 of the disease and 53% were in Stage 2. Forty-three percent of patients had Val30Met mutations in the transthyretin gene; the remaining patients had 38 other point mutations. Sixty-two percent of ONPATTRO-treated patients had non-Val30Met mutations, compared to 48% of the placebo-treated patients.

Upper respiratory tract infections and infusion-related reactions were the most common adverse reactions. One patient (0.7%) discontinued ONPATTRO because of an infusion-related reaction.

Patients were instructed to take the recommended daily allowance of vitamin A [see Warnings and Precautions (5.2)]. Sixty-four percent of patients treated with ONPATTRO had normal vitamin A levels at baseline, and 99% of those with a normal baseline developed low vitamin A levels. In one case, the decreased vitamin A level was reported as an adverse reaction.

Table 1 lists the adverse reactions that occurred in at least 5% of patients in the ONPATTRO-treated group and that occurred at least 3% more frequently than in the placebo-treated group in the randomized controlled clinical trial.

Table 1: Adverse Reactions from the Placebo-Controlled Trial that Occurred in at Least 5% of ONPATTRO-treated Patients and at Least 3% More Frequently than in Placebo-treated Patients
Adverse Reaction | ONPATTRO N=148 % | Placebo N=77 %
Upper respiratory tract infections [Includes nasopharyngitis, upper respiratory tract infection, respiratory tract infection, pharyngitis, rhinitis, sinusitis, viral upper respiratory tract infection, upper respiratory tract congestion.] | 29 | 21
Infusion-related reaction [Infusion-related reaction symptoms include, but are not limited to: arthralgia or pain (including back, neck, or musculoskeletal pain), flushing (including erythema of face or skin warm), nausea, abdominal pain, dyspnea or cough, chest discomfort or chest pain, headache, rash, chills, dizziness, fatigue, increased heart rate or palpitations, hypotension, hypertension, facial edema.] | 19 | 9
Dyspepsia | 8 | 4
Dyspnea [Not part of an infusion-related reaction.] , [Includes dyspnea and exertional dyspnea.] | 8 | 0
Muscle spasms | 8 | 1
Arthralgia | 7 | 0
Erythema | 7 | 3
Bronchitis [Includes bronchitis, bronchiolitis, bronchitis viral, lower respiratory tract infection, lung infection.] | 7 | 3
Vertigo | 5 | 1

Four serious adverse reactions of atrioventricular (AV) heart block (2.7%) occurred in ONPATTRO-treated patients, including 3 cases of complete AV block. No serious adverse reactions of AV block were reported in placebo-treated patients.

Ocular adverse reactions that occurred in 5% or less of ONPATTRO-treated patients in the controlled clinical trial, but in at least 2% of ONPATTRO-treated patients, and more frequently than on placebo, include dry eye (5% vs. 3%), blurred vision (3% vs. 1%), and vitreous floaters (2% vs. 1%).

Extravasation was observed in less than 0.5% of infusions in clinical studies, including cases that were reported as serious. Signs and symptoms included phlebitis or thrombophlebitis, infusion or injection site swelling, dermatitis (subcutaneous inflammation), cellulitis, erythema or injection site redness, burning sensation, or injection site pain.

6.2 Immunogenicity

The detection of antibody formation is highly dependent on the sensitivity and specificity of the assay. In addition, the observed incidence of antibody (including neutralizing antibody) positivity in an assay may be influenced by several factors, including assay methodology, sample handling, timing of sample collection, concomitant medications, and underlying disease. For these reasons, comparison of the incidence of antibodies to ONPATTRO in the studies described below with the incidence of antibodies in other studies or to other products may be misleading.

Anti-drug antibodies to ONPATTRO were evaluated by measuring antibodies specific to PEG2000-C-DMG, a lipid component exposed on the surface of ONPATTRO. In the placebo-controlled and open-label clinical studies, 7 of 194 (3.6%) patients with hATTR amyloidosis developed anti-drug antibodies during treatment with ONPATTRO. One additional patient had pre-existing anti-drug antibodies. There was no evidence of an effect of anti-drug antibodies on clinical efficacy, safety, or the pharmacokinetic or pharmacodynamic profiles of ONPATTRO. Although these data do not demonstrate an impact of anti-drug antibody development on the efficacy or safety of ONPATTRO in these patients, the available data are too limited to make definitive conclusions.

6.3 Postmarketing Experience

The following adverse reactions have been identified during postapproval use of ONPATTRO. Because these reactions are reported voluntarily from a population of uncertain size, it is not always possible to reliably estimate their frequency or establish a causal relationship to drug exposure.

Symptoms of infusion-related reactions have included syncope [see Warnings and Precautions (5.1)] and pruritus.

8 USE IN SPECIFIC POPULATIONS

8.1 Pregnancy

Pregnancy Exposure Registry

There is a pregnancy exposure registry that monitors pregnancy outcomes in women exposed to ONPATTRO during pregnancy. Physicians are encouraged to enroll pregnant patients, or pregnant women may register themselves in the program by calling 1-877-256-9526 or by contacting alnylampregnancyprogram@iqvia.com.

Risk Summary

There are no available data on ONPATTRO use in pregnant women to inform a drug-associated risk of adverse developmental outcomes. ONPATTRO treatment leads to a decrease in serum vitamin A levels, and vitamin A supplementation is advised for patients taking ONPATTRO. Vitamin A is essential for normal embryofetal development; however, excessive levels of vitamin A are associated with adverse developmental effects. The effects on the fetus of a reduction in maternal serum TTR caused by ONPATTRO and of vitamin A supplementation are unknown [see Clinical Pharmacology (12.2), Warnings and Precautions (5.2)].

In animal studies, intravenous administration of patisiran lipid complex (patisiran-LC) to pregnant rabbits resulted in developmental toxicity (embryofetal mortality and reduced fetal body weight) at doses that were also associated with maternal toxicity. No adverse developmental effects were observed when patisiran-LC or a rodent-specific (pharmacologically active) surrogate were administered to pregnant rats (see Data).

In the U.S. general population, the estimated background risk of major birth defects and miscarriage in clinically recognized pregnancies is 2 to 4% and 15 to 20%, respectively. The background risk of major birth defects and miscarriage for the indicated population is unknown.

Data

Animal Data

Intravenous administration of patisiran-LC (0, 0.15, 0.50, or 1.5 mg/kg) or a rodent-specific (pharmacologically active) surrogate (1.5 mg/kg) to female rats every week for two weeks prior to mating and continuing throughout organogenesis resulted in no adverse effects on fertility or embryofetal development.

Intravenous administration of patisiran-LC (0, 0.1, 0.3, or 0.6 mg/kg) to pregnant rabbits every week during the period of organogenesis produced no adverse effects on embryofetal development. In a separate study, patisiran-LC (0, 0.3, 1, or 2 mg/kg), administered to pregnant rabbits every week during the period of organogenesis, resulted in embryofetal mortality and reduced fetal body weight at the mid and high doses, which were associated with maternal toxicity.

Intravenous administration of patisiran-LC (0, 0.15, 0.50, or 1.5 mg/kg) or a rodent-specific surrogate (1.5 mg/kg) to pregnant rats every week throughout pregnancy and lactation resulted in no adverse developmental effects on the offspring.

8.2 Lactation

Risk Summary

There is no information regarding the presence of ONPATTRO in human milk, the effects on the breastfed infant, or the effects on milk production. The developmental and health benefits of breastfeeding should be considered along with the mother's clinical need for ONPATTRO and any potential adverse effects on the breastfed infant from ONPATTRO or from the underlying maternal condition.

In lactating rats, patisiran was not detected in milk; however, the lipid components (DLin-MC3-DMA and PEG2000-C-DMG) were present in milk.

8.4 Pediatric Use

Safety and effectiveness in pediatric patients have not been established.

8.5 Geriatric Use

No dose adjustment is required in patients ≥65 years old [see Clinical Pharmacology (12.3)]. A total of 62 patients ≥65 years of age, including 9 patients ≥75 years of age, received ONPATTRO in the placebo-controlled study. No overall differences in safety or effectiveness were observed between these patients and younger patients, but greater sensitivity of some older individuals cannot be ruled out.

8.6 Hepatic Impairment

No dose adjustment is necessary in patients with mild hepatic impairment (bilirubin ≤1 × ULN and AST >1 × ULN, or bilirubin >1.0 to 1.5 × ULN) [see Clinical Pharmacology (12.3)]. ONPATTRO has not been studied in patients with moderate or severe hepatic impairment.

8.7 Renal Impairment

No dose adjustment is necessary in patients with mild or moderate renal impairment (estimated glomerular filtration rate [eGFR] ≥30 to <90 mL/min/1.73m^2) [see Clinical Pharmacology (12.3)]. ONPATTRO has not been studied in patients with severe renal impairment or end-stage renal disease.

11 DESCRIPTION

ONPATTRO contains patisiran, a double-stranded small interfering ribonucleic acid (siRNA), formulated as a lipid complex for delivery to hepatocytes. Patisiran specifically binds to a genetically conserved sequence in the 3' untranslated region (3'UTR) of mutant and wild-type transthyretin (TTR) messenger RNA (mRNA).

The structural formula is:

A, adenosine; C, cytidine; G, guanosine; U, uridine; Cm, 2'-O-methylcytidine; Um, 2'-O-methyluridine; dT, thymidine

ONPATTRO is supplied as a sterile, preservative-free, white to off-white, opalescent, homogeneous solution for intravenous infusion in a single-dose glass vial. Each 1 mL of solution contains 2 mg of patisiran (equivalent to 2.1 mg of patisiran sodium). Each 1 mL also contains 6.2 mg cholesterol USP, 13.0 mg (6Z,9Z,28Z,31Z)-heptatriaconta-6,9,28,31-tetraen-19-yl-4-(dimethylamino) butanoate (DLin-MC3-DMA), 3.3 mg 1,2-distearoyl-sn-glycero-3-phosphocholine (DSPC), 1.6 mg α-(3'-{[1,2-di(myristyloxy)propanoxy] carbonylamino}propyl)-ω-methoxy, polyoxyethylene (PEG2000-C-DMG), 0.2 mg potassium phosphate monobasic anhydrous NF, 8.8 mg sodium chloride USP, 2.3 mg sodium phosphate dibasic heptahydrate USP, and Water for Injection USP. The pH is ~7.0.

The molecular formula of patisiran sodium is C412 H480 N148 Na40 O290 P40 and the molecular weight is 14304 Da.

12 CLINICAL PHARMACOLOGY

12.1 Mechanism of Action

Patisiran is a double-stranded siRNA that causes degradation of mutant and wild-type TTR mRNA through RNA interference, which results in a reduction of serum TTR protein and TTR protein deposits in tissues.

12.2 Pharmacodynamics

The pharmacodynamic effects of ONPATTRO were evaluated in hATTR amyloidosis patients treated with 0.3 mg/kg ONPATTRO via intravenous infusion once every 3 weeks.

Mean serum TTR was reduced by approximately 80% within 10 to 14 days after a single dose. With repeat dosing every 3 weeks, mean reductions of serum TTR after 9 and 18 months of treatment were 83% and 84%, respectively. The mean maximum reduction of serum TTR over 18 months was 88%. Similar TTR reductions were observed regardless of TTR mutation, sex, age, race, or prior liver transplantation. In a dose-ranging study, greater TTR reduction was maintained over the dosing interval with the recommended dosing regimen of 0.3 mg/kg every 3 weeks compared to 0.3 mg/kg every 4 weeks.

Serum TTR is a carrier of retinol binding protein, which is involved in the transport of vitamin A in the blood. Mean reductions in serum retinol binding protein of 45% and serum vitamin A of 62% were observed over 18 months [see Warnings and Precautions (5.2)].

12.3 Pharmacokinetics

Following a single intravenous administration, systemic exposure to patisiran increases in a linear and dose-proportional manner over the range of 0.01 to 0.5 mg/kg. Greater than 95% of patisiran in the circulation is associated with the lipid complex. At the recommended dosing regimen of 0.3 mg/kg every 3 weeks, steady state is reached by 24 weeks of treatment. The estimated mean ± SD steady state peak concentrations (Cmax), trough concentrations (Ctrough), and area under the curve (AUCτ) were 7.15 ± 2.14 µg/mL, 0.021 ± 0.044 µg/mL, and 184 ± 159 µg∙h/mL, respectively. The accumulation of AUCτ was 3.2-fold at steady state, compared to the first dose. In the placebo-controlled study, inter-patient variability in patisiran exposure did not result in differences in clinical efficacy (mNIS+7 change from baseline) or safety (adverse events, serious adverse events).

Distribution

Plasma protein binding of ONPATTRO is low, with ≤2.1% binding observed in vitro with human serum albumin and human α1-acid glycoprotein. ONPATTRO distributes primarily to the liver. At the recommended dosing regimen of 0.3 mg/kg every 3 weeks, the mean ± SD steady state volume of distribution of patisiran (Vss) was 0.26 ± 0.20 L/kg.

Elimination

The terminal elimination half-life (mean ± SD) of patisiran is 3.2 ± 1.8 days. Patisiran is mainly cleared through metabolism, and the total body clearance (mean ± SD) at steady state (CLss) is 3.0 ± 2.5 mL/h/kg.

Metabolism

Patisiran is metabolized by nucleases to nucleotides of various lengths.

Excretion

Less than 1% of the administered dose of patisiran is excreted unchanged into urine.

Specific Populations

Age, race (non-Caucasian vs. Caucasian), sex, and prior liver transplantation had no impact on the steady state pharmacokinetics of patisiran or TTR reduction. Population pharmacokinetic and pharmacodynamic analyses indicated no impact of mild or moderate renal impairment (eGFR ≥30 to <90 mL/min/1.73m^2) or mild hepatic impairment (bilirubin ≤1 × ULN and AST >1 × ULN, or bilirubin >1.0 to 1.5 × ULN) on patisiran exposure or TTR reduction. ONPATTRO has not been studied in patients with severe renal impairment, end-stage renal disease, or moderate or severe hepatic impairment.

Drug Interaction Studies

No formal clinical drug interaction studies have been performed. The components of ONPATTRO are not inhibitors or inducers of cytochrome P450 enzymes or transporters at clinically relevant plasma concentrations. Patisiran is not a substrate of cytochrome P450 enzymes. In a population pharmacokinetic analysis, concomitant use of strong or moderate CYP3A inducers and inhibitors did not impact the pharmacokinetic parameters of patisiran. ONPATTRO is not expected to cause drug-drug interactions or to be affected by inhibitors or inducers of cytochrome P450 enzymes.

13 NONCLINICAL TOXICOLOGY

13.1 Carcinogenesis, Mutagenesis, Impairment of Fertility

Carcinogenesis

Patisiran-LC was not carcinogenic in TgRasH2 mice when administered at intravenous (IV) doses of 0, 0.5, 2, or 6 mg/kg every two weeks for 26 weeks.

Mutagenesis

Patisiran-LC was negative for genotoxicity in in vitro (bacterial mutagenicity assay, chromosomal aberration assay in human peripheral blood lymphocytes) and in vivo (mouse bone marrow micronucleus) assays.

Impairment of Fertility

Intravenous (IV) administration of patisiran-LC (0, 0.03, 0.1, or 0.3 mg/kg) or a rodent-specific (pharmacologically active) surrogate (0.1 mg/kg) to male rats every two weeks prior to and throughout mating to untreated females produced no adverse effects on fertility.

Intravenous administration of patisiran-LC (0, 0.15, 0.50, or 1.5 mg/kg) or a rodent-specific (pharmacologically active) surrogate (1.5 mg/kg) to female rats every week for two weeks prior to mating and continuing throughout organogenesis resulted in no adverse effects on fertility or on embryofetal development.

Intravenous administration of patisiran-LC (0, 0.3, 1, or 2 mg/kg) to adult monkeys every three weeks for 39 weeks produced no adverse effects on male reproductive organs or on sperm morphology or count.

14 CLINICAL STUDIES

The efficacy of ONPATTRO was demonstrated in a randomized, double-blind, placebo-controlled, multicenter clinical trial in adult patients with polyneuropathy caused by hATTR amyloidosis (NCT 01960348). Patients were randomized in a 2:1 ratio to receive ONPATTRO 0.3 mg/kg (N=148) or placebo (N=77), respectively, via intravenous infusion once every 3 weeks for 18 months. All patients received premedication with a corticosteroid, acetaminophen, and H1 and H2 blockers. Ninety-three percent of ONPATTRO-treated patients and 62% of placebo-treated patients completed 18 months of the assigned treatment.

The primary efficacy endpoint was the change from baseline to Month 18 in the modified Neuropathy Impairment Score +7 (mNIS+7). The mNIS+7 is an objective assessment of neuropathy and comprises the NIS and Modified +7 (+7) composite scores. In the version of the mNIS+7 used in the trial, the NIS objectively measures deficits in cranial nerve function, muscle strength, and reflexes, and the +7 assesses postural blood pressure, quantitative sensory testing, and peripheral nerve electrophysiology. The maximum possible score was 304 points, with higher scores representing a greater severity of disease.

The clinical meaningfulness of effects on the mNIS+7 was assessed by the change from baseline to Month 18 in Norfolk Quality of Life-Diabetic Neuropathy (QoL-DN) total score. The Norfolk QoL-DN scale is a patient-reported assessment that evaluates the subjective experience of neuropathy in the following domains: physical functioning/large fiber neuropathy, activities of daily living, symptoms, small fiber neuropathy, and autonomic neuropathy. The version of the Norfolk QoL-DN that was used in the trial had a total score range from -4 to 136, with higher scores representing greater impairment.

The changes from baseline to Month 18 on both the mNIS+7 and the Norfolk QoL-DN significantly favored ONPATTRO (Table 2, Figure 1 and Figure 3). The distributions of changes in mNIS+7 and Norfolk QoL-DN scores from baseline to Month 18 by percent of patients are shown in Figure 2 and Figure 4, respectively.

The changes from baseline to Month 18 in modified body mass index (mBMI) and gait speed (10-meter walk test) significantly favored ONPATTRO (Table 2).

Table 2: Clinical Efficacy Results from the Placebo-Controlled Study
Endpoint [All endpoints analyzed using the mixed-effect model repeated measures (MMRM) method.] | Baseline, Mean (SD) |  | Change from Baseline to Month 18, LS Mean (SEM) |  | ONPATTRO-Placebo Treatment Difference, LS Mean (95% CI) | p-value
Endpoint [All endpoints analyzed using the mixed-effect model repeated measures (MMRM) method.] | ONPATTRO N=148 | Placebo N=77 | ONPATTRO | Placebo | ONPATTRO-Placebo Treatment Difference, LS Mean (95% CI) | p-value
Primary
mNIS+7 [A lower value indicates less impairment/fewer symptoms.] | 80.9 (41.5) | 74.6 (37.0) | -6.0 (1.7) | 28.0 (2.6) | -34.0 (-39.9, -28.1) | p<0.001
Secondary
Norfolk QoL-DN | 59.6 (28.2) | 55.5 (24.3) | -6.7 (1.8) | 14.4 (2.7) | -21.1 (-27.2, -15.0) | p<0.001
10-meter walk test (m/sec) [A higher number indicates less disability/less impairment.] | 0.80 (0.40) | 0.79 (0.32) | 0.08 (0.02) | -0.24 (0.04) | 0.31 (0.23, 0.39) | p<0.001
mBMI [mBMI: body mass index (BMI; kg/m^2) multiplied by serum albumin (g/L); a higher number indicates better nutritional status.] | 970 (210) | 990 (214) | -3.7 (9.6) | -119 (14.5) | 116 (82, 149) | p<0.001
CI, confidence interval; LS, least squares; mBMI, modified body mass index; mNIS, modified Neuropathy Impairment Score; QoL-DN, Quality of Life – Diabetic Neuropathy; SD, standard deviation; SEM, standard error of the mean

Figure 1: Change from Baseline in mNIS+7

A decrease in mNIS+7 indicates improvement.

Δ indicates between-group treatment difference, shown as the LS mean difference (95% CI) for ONPATTRO – placebo.

Figure 2: Histogram of mNIS+7 Change from Baseline at Month 18

mNIS+7 change scores are rounded to the nearest whole number; last available post-baseline scores were used.

Categories are mutually exclusive; patients who died before 18 months are summarized in the "Death" category only.

Figure 3: Change from Baseline in Norfolk QoL-DN Score

A decrease in Norfolk QoL-DN score indicates improvement.

Δ indicates between-group treatment difference, shown as the LS mean difference (95% CI) for ONPATTRO – placebo.

Figure 4: Histogram of Norfolk QoL-DN Change from Baseline at Month 18

Norfolk QoL-DN change scores are rounded to the nearest whole number; last available post-baseline scores were used.

Categories are mutually exclusive; patients who died before 18 months are summarized in the "Death" category only.

Patients receiving ONPATTRO experienced similar improvements relative to placebo in mNIS+7 and Norfolk QoL-DN score across all subgroups including age, sex, race, region, NIS score, Val30Met mutation status, and disease stage.

16 HOW SUPPLIED/STORAGE AND HANDLING

16.1 How Supplied

ONPATTRO is a sterile, preservative-free, white to off-white, opalescent, homogeneous solution for intravenous infusion supplied as a 10 mg/5 mL (2 mg/mL) solution in a single-dose glass vial. The vial stopper is not made with natural rubber latex. ONPATTRO is available in cartons containing one single-dose vial each.

The NDC is: 71336-1000-1.

16.2 Storage and Handling

Store at 2°C to 8°C (36°F to 46°F). Do not freeze. Discard vial if it has been frozen.

If refrigeration is not available, ONPATTRO can be stored at room temperature up to 25°C (up to 77°F) for up to 14 days.

For storage conditions of ONPATTRO after dilution in the infusion bag, see Dosage and Administration (2.3).

17 PATIENT COUNSELING INFORMATION

Infusion-Related Reactions

Inform patients about the signs and symptoms of infusion-related reactions (e.g., flushing, dyspnea, chest pain, syncope, rash, increased heart rate, facial edema). Advise patients to contact their healthcare provider immediately if they experience signs and symptoms of infusion-related reactions [see Warnings and Precautions (5.1)].

Recommended Vitamin A Supplementation

Inform patients that ONPATTRO treatment leads to a decrease in vitamin A levels measured in the serum. Instruct patients to take the recommended daily allowance of vitamin A. Advise patients to contact their healthcare provider if they experience ocular symptoms suggestive of vitamin A deficiency (e.g., night blindness) and refer them to an ophthalmologist if they develop these symptoms [see Warnings and Precautions (5.2)].

Pregnancy

Instruct patients that if they are pregnant or plan to become pregnant while taking ONPATTRO they should inform their healthcare provider. Advise female patients of childbearing potential of the potential risk to the fetus. Encourage patients to enroll in the ONPATTRO pregnancy exposure registry if they become pregnant while taking ONPATTRO [see Use in Specific Populations (8.1)].

Manufactured for: Alnylam Pharmaceuticals, Inc.
300 Third Street, Cambridge, MA 02142
By: PCI San Diego, Inc.
11040 Roselle Street, San Diego, CA 92121

ONPATTRO is a registered trademark of Alnylam Pharmaceuticals, Inc.

PRINCIPAL DISPLAY PANEL - 2 mg/mL Vial Carton

NDC 71336-1000-1

onpattro®
(patisiran)
lipid complex injection

10 mg/5 mL
(2 mg/mL)

Sterile Solution for
Intravenous Infusion Only

Dilute Before Use

Single-Dose Vial

Discard Unused Portion

Rx Only